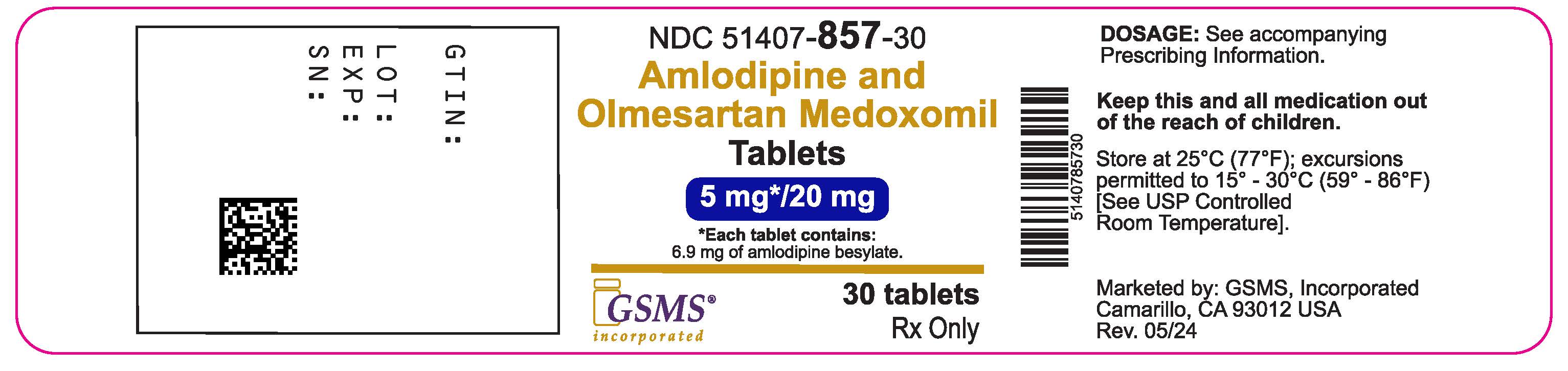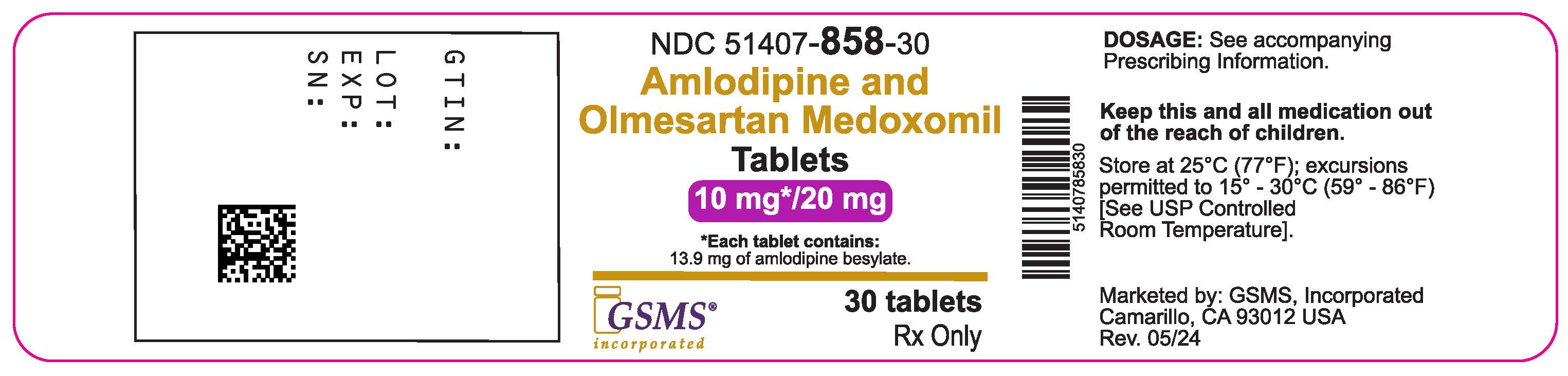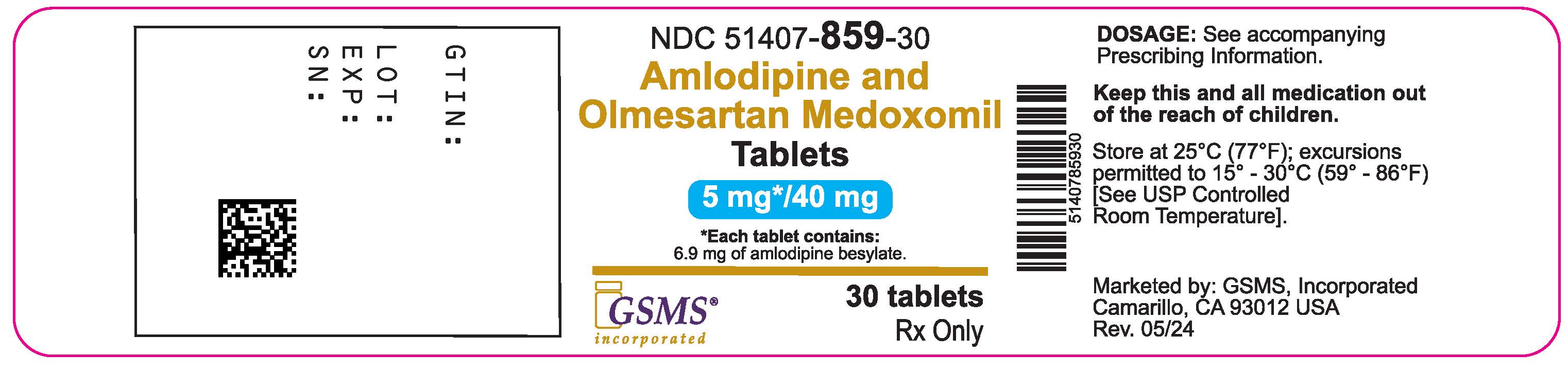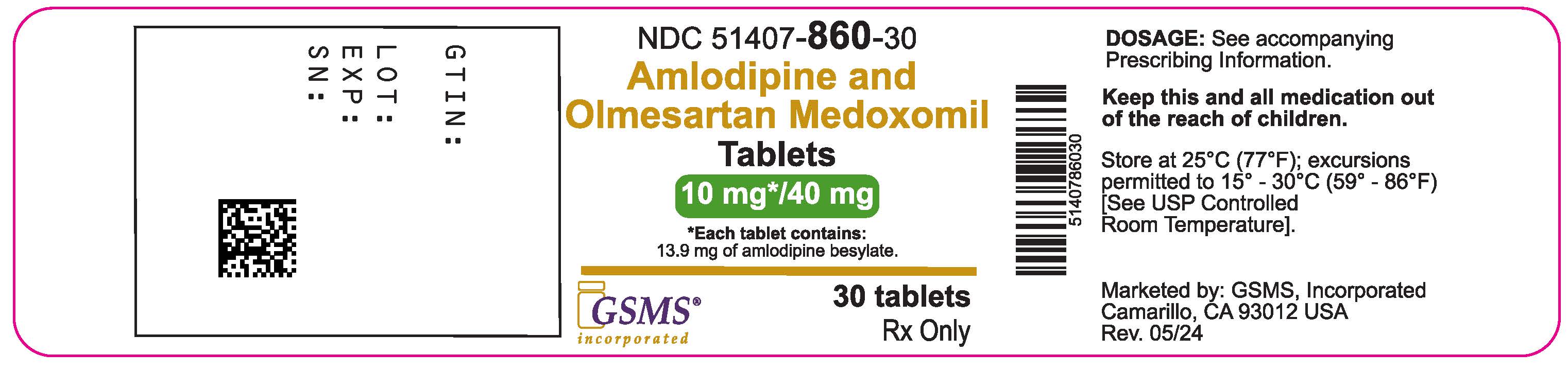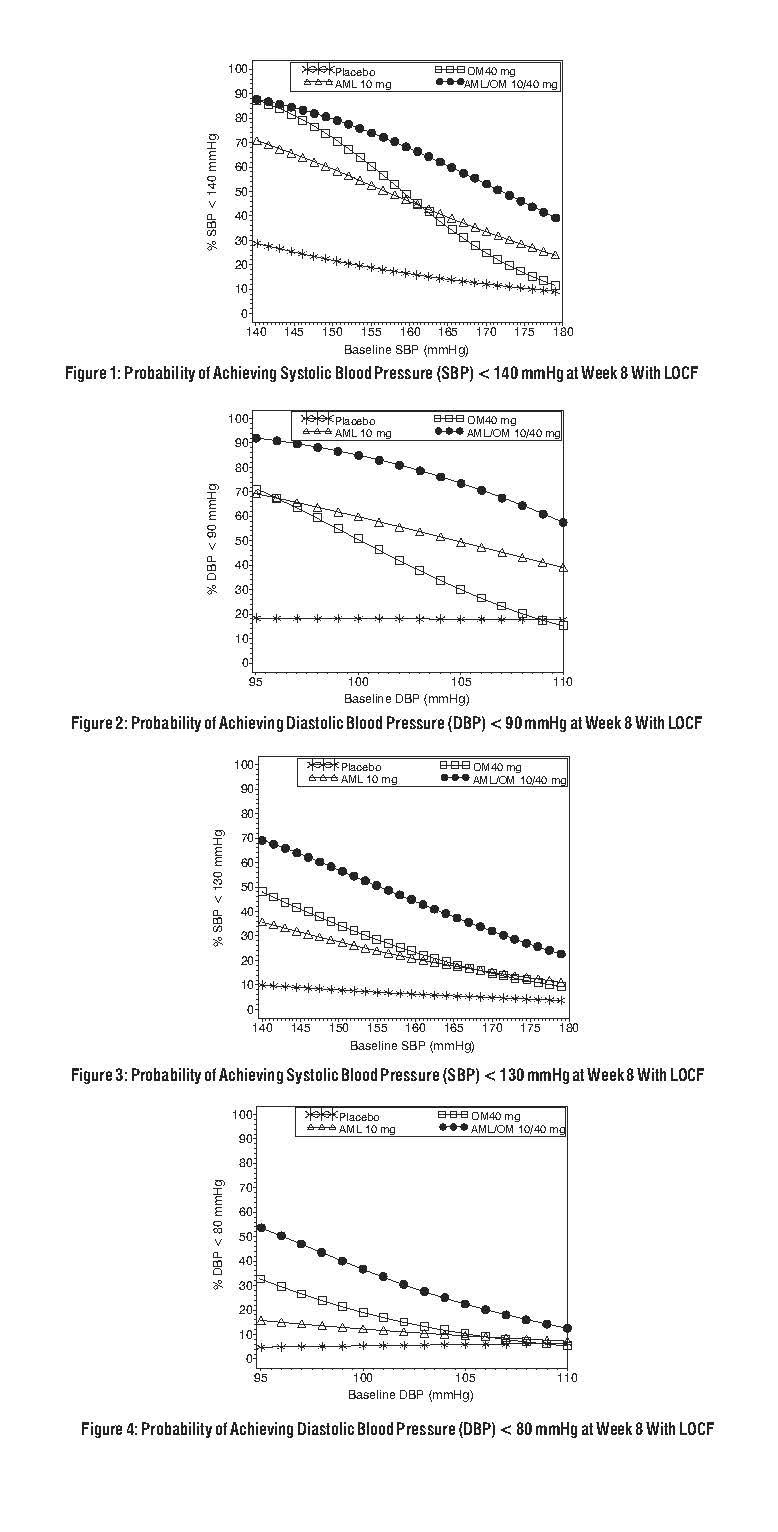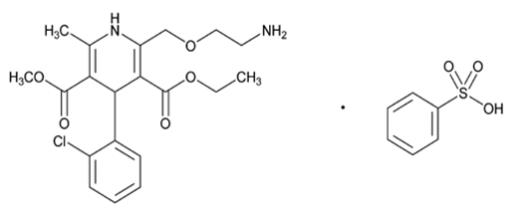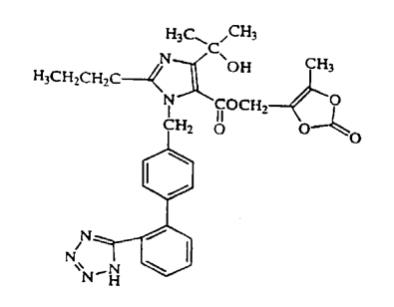 DRUG LABEL: amlodipine besylate and olmesartan medoxomil
NDC: 51407-858 | Form: TABLET, FILM COATED
Manufacturer: Golden State Medical Supply, Inc.
Category: prescription | Type: HUMAN PRESCRIPTION DRUG LABEL
Date: 20240603

ACTIVE INGREDIENTS: AMLODIPINE BESYLATE 10 mg/1 1; OLMESARTAN MEDOXOMIL 20 mg/1 1
INACTIVE INGREDIENTS: MICROCRYSTALLINE CELLULOSE; STARCH, CORN; CROSCARMELLOSE SODIUM; MAGNESIUM STEARATE; POLYVINYL ALCOHOL, UNSPECIFIED; POLYETHYLENE GLYCOL 3350; TITANIUM DIOXIDE; TALC; FERRIC OXIDE RED; FERROSOFERRIC OXIDE; FERRIC OXIDE YELLOW

HIGHLIGHTS OF PRESCRIBING INFORMATION

Amlodipine besylate and olmesartan medoxomil. These highlights do not include all the information needed to useamlodipine besylate and olmesartan medoxomil safely and effectively. See full prescribing information for amlodipine besylate and olmesartan medoxomil.
Amlodipine and olmesartan medoxomil tablets, for oral use
Initial U.S. Approval: 2007

WARNING: FETAL TOXICITY

See full prescribing information for complete boxed warning.

- When pregnancy is detected, discontinue amlodipine besylate and olmesartan medoxomil as soon as possible (5.1, 8.1).
- Drugs that act directly on the renin-angiotensin system can cause injury and death to the developing fetus (5.1, 8.1).

1 INDICATIONS AND USAGE

- Amlodipine besylate and olmesartan medoxomil is a combination of amlodipine besylate, a dihydropyridine calcium channel blocker, and olmesartan medoxomil, an angiotensin II receptor blocker, indicated for the treatment of hypertension, alone or with other antihypertensive agents, to lower blood pressure. Lowering blood pressure reduces the risk of fatal and nonfatal cardiovascular events, primarily strokes and myocardial infarctions (1).
- Amlodipine besylate and olmesartan medoxomil may also be used as initial therapy in patients likely to need multiple antihypertensive agents to achieve their blood pressure goals (1).

2 DOSAGE AND ADMINISTRATION

- Recommended starting dose: 5/20 mg once daily (2).
- Titrate as needed in two-week intervals up to a maximum of 10/40 mg once daily (2).

3 DOSAGE FORMS AND STRENGTHS

Tablets: (amlodipine/olmesartan medoxomil content) 5/20 mg, 10/20 mg, 5/40 mg, and 10/40 mg (3).

4 CONTRAINDICATIONS

- Do not co-administer aliskiren with amlodipine besylate and olmesartan medoxomil in patients with diabetes (4).

5 WARNINGS AND PRECAUTIONS

- Anticipate hypotension in volume- or salt-depleted patients with treatment initiation. Start treatment under close supervision (5.2).
- Increased angina or myocardial infarction may occur upon dosage initiation or increase (5.3).
- Impaired renal function: changes in renal function may occur (5.4).
- Sprue-like enteropathy has been reported. Consider discontinuation of amlodipine besylate and olmesartan medoxomil in cases where no other etiology is found (5.6).

6 ADVERSE REACTIONS

Most common adverse reaction (incidence ≥3%) is edema (6.1).

To report SUSPECTED ADVERSE REACTIONS, contact Cosette Pharmaceuticals, Inc. at 1-800-922-1038 or FDA at 1-800-FDA-1088 or www.fda.gov/medwatch.

7 DRUG INTERACTIONS

Amlodipine (7.1):

- If simvastatin is co-administered with amlodipine, do not exceed 20 mg daily of simvastatin.
- Increased exposure of cyclosporine and tacrolimus.
- Increased exposure of amlodipine when coadministered with CYP3A inhibitors.

Olmesartan medoxomil (7.2):

- Nonsteroidal anti-inflammatory drugs (NSAIDS) may lead to increased risk of renal impairment and loss of antihypertensive effect.
- Dual inhibition of the renin-angiotensin system: Increased risk of renal impairment, hypotension, and hyperkalemia.
- Colesevelam hydrochloride: Consider administering olmesartan at least 4 hours before colesevelam hydrochloride dose.
- Lithium: Increases in serum lithium concentrations and lithium toxicity.

8 USE IN SPECIFIC POPULATIONS

- Lactation: Breastfeeding is not recommended (8.2).
- Geriatric: Not recommended for initial therapy in patients ≥75 years old (8.5)
- Hepatic Impairment: Not recommended for initial therapy (8.6).

FULL PRESCRIBING INFORMATION

WARNING: FETAL TOXICITY

- When pregnancy is detected, discontinue amlodipine besylate and olmesartan medoxomil as soon as possible (5.1, 8.1).
- Drugs that act directly on the renin-angiotensin system (RAS) can cause injury and death to the developing fetus (5.1, 8.1).

1 INDICATIONS AND USAGE

Amlodipine besylate and olmesartan medoxomil is indicated for the treatment of hypertension, alone or with other antihypertensive agents, to lower blood pressure. Lowering blood pressure reduces the risk of fatal and nonfatal cardiovascular (CV) events, primarily strokes and myocardial infarctions. These benefits have been seen in controlled trials of antihypertensive drugs from a wide variety of pharmacologic classes including the class to which this drug principally belongs. There are no controlled trials demonstrating risk reduction with amlodipine besylate and olmesartan medoxomil.

Control of high blood pressure should be part of comprehensive cardiovascular risk management, including, as appropriate, lipid control, diabetes management, antithrombotic therapy, smoking cessation, exercise, and limited sodium intake. Many patients will require more than one drug to achieve blood pressure goals. For specific advice on goals and management, see published guidelines, such as those of the National High Blood Pressure Education Program’s Joint National Committee on Prevention, Detection, Evaluation, and Treatment of High Blood Pressure (JNC).

Numerous antihypertensive drugs, from a variety of pharmacologic classes and with different mechanisms of action, have been shown in randomized controlled trials to reduce cardiovascular morbidity and mortality, and it can be concluded that it is blood pressure reduction, and not some other pharmacologic property of the drugs, that is largely responsible for those benefits. The largest and most consistent cardiovascular outcome benefit has been a reduction in the risk of stroke, but reductions in myocardial infarction and cardiovascular mortality also have been seen regularly.

Elevated systolic or diastolic pressure causes increased cardiovascular risk, and the absolute risk increase per mmHg is greater at higher blood pressures, so that even modest reductions of severe hypertension can provide substantial benefit. Relative risk reduction from blood pressure reduction is similar across populations with varying absolute risk, so the absolute benefit is greater in patients who are at higher risk independent of their hypertension (for example, patients with diabetes or hyperlipidemia), and such patients would be expected to benefit from more aggressive treatment to a lower blood pressure goal.

Some antihypertensive drugs have smaller blood pressure effects (as monotherapy) in black patients, and many antihypertensive drugs have additional approved indications and effects (e.g., on angina, heart failure, or diabetic kidney disease). These considerations may guide selection of therapy.

Amlodipine besylate and olmesartan medoxomil may also be used as initial therapy in patients who are likely to need multiple antihypertensive agents to achieve their blood pressure goals.

Patients with moderate or severe hypertension are at relatively high risk for cardiovascular events (such as strokes, heart attacks, and heart failure), kidney failure, and vision problems, so prompt treatment is clinically relevant. The decision to use a combination as initial therapy should be individualized and should be shaped by considerations such as baseline blood pressure, the target goal, and the incremental likelihood of achieving goal with a combination compared to monotherapy. Individual blood pressure goals may vary based upon the patient’s risk.

Data from an 8-week, placebo-controlled, parallel-group factorial study [see Clinical Studies (14.1)] provide estimates of the probability of reaching a blood pressure goal with amlodipine besylate and olmesartan medoxomil compared to amlodipine or olmesartan medoxomil monotherapy. The figures below provide estimates of the likelihood of achieving the targeted systolic or diastolic blood pressure goals with amlodipine besylate and olmesartan medoxomil 10/40 mg compared with amlodipine or olmesartan medoxomil monotherapy, based upon baseline systolic or diastolic blood pressure. The curve of each treatment group was estimated by logistic regression modeling from all available data of that treatment group. The right tail of each curve is less reliable because of small numbers of subjects with high baseline blood pressures.

The figures above provide an approximation of the likelihood of reaching a targeted blood pressure goal (e.g., Week 8 SBP <140 mmHg or <130 mmHg or a DBP <90 mmHg or <80 mmHg) for the high-dose treatment groups evaluated in the study. Amlodipine besylate and olmesartan medoxomil 5/20 mg, the lowest dose combination treatment group, increases the probability of reaching blood pressure goal compared with the highest dose monotherapies, amlodipine 10 mg and olmesartan medoxomil 40 mg.

For example, a patient with a baseline blood pressure of 160/100 mmHg has about a 48% likelihood of achieving a goal of <140 mmHg (systolic) and a 51% likelihood of achieving a goal of <90 mmHg (diastolic) on monotherapy with olmesartan medoxomil 40 mg, and about a 46% likelihood of achieving a goal of <140 mmHg (systolic) and a 60% likelihood of achieving a goal of <90 mmHg (diastolic) on monotherapy with amlodipine 10 mg. The likelihood of achieving these same goals increases to 63% (systolic) and 71% (diastolic) on amlodipine besylate and olmesartan medoxomil 5/20 mg, and to 68% (systolic) and 85% (diastolic) on amlodipine besylate and olmesartan medoxomil 10/40 mg.

2 DOSAGE AND ADMINISTRATION

The usual starting dose of amlodipine besylate and olmesartan medoxomil is 5/20 mg once daily. The dosage can be increased after 1 to 2 weeks of therapy to a maximum dose of one 10/40 mg tablet once daily as needed to control blood pressure [see Clinical Studies (14.1)].

3 DOSAGE FORMS AND STRENGTHS

Amlodipine besylate and olmesartan medoxomil tablets are formulated for oral administration in the following strength combinations:

Amlodipine equivalent: 5/20 - 5mg; 5/40 - 5mg; 10/20 - 10mg; 10/40 - 10mg

Olmesartan medoxomil: 5/20 - 20mg; 5/40 - 40mg; 10/20 - 20mg; 10/40 - 40mg

4 CONTRAINDICATIONS

Do not co-administer aliskiren with amlodipine besylate and olmesartan medoxomil in patients with diabetes [see Drug Interactions (7.2)].

5 WARNINGS AND PRECAUTIONS

5.1 Fetal Toxicity

Amlodipine besylate and olmesartan medoxomil can cause fetal harm when administered to a pregnant woman. Use of drugs that act on the renin-angiotensin system during the second and third trimesters of pregnancy reduces fetal renal function and increases fetal and neonatal morbidity and death. Resulting oligohydramnios can be associated with fetal lung hypoplasia and skeletal deformations. Potential neonatal adverse effects include skull hypoplasia, anuria, hypotension, renal failure, and death. When pregnancy is detected, discontinue amlodipine besylate and olmesartan medoxomil as soon as possible [see Use in Specific Populations (8.1)].

5.2 Hypotension in Volume- or Salt-Depleted Patients

Olmesartan medoxomil. In patients with an activated renin-angiotensin system, such as volume- and/or salt-depleted patients (e.g., those being treated with high doses of diuretics) symptomatic hypotension may be anticipated after initiation of treatment with olmesartan medoxomil. Initiate treatment with amlodipine besylate and olmesartan medoxomil under close medical supervision. If hypotension does occur, place the patient in the supine position and, if necessary, give an intravenous infusion of normal saline. A transient hypotensive response is not a contraindication to further treatment, which usually can be continued without difficulty once the blood pressure has stabilized.

Amlodipine. Symptomatic hypotension is possible, particularly in patients with severe aortic stenosis. Because of the gradual onset of action, acute hypotension is unlikely.

5.3 Increased Angina or Myocardial Infarction

Patients, particularly those with severe obstructive coronary artery disease, may develop increased frequency, duration, or severity of angina or acute myocardial infarction on starting calcium channel blocker therapy or at the time of dosage increase. The mechanism of this effect has not been elucidated.

5.4 Impaired Renal Function

Changes in renal function may be anticipated in susceptible individuals treated with olmesartan medoxomil as a consequence of inhibiting the renin-angiotensin-aldosterone system. In patients whose renal function may depend upon the activity of the renin-angiotensin-aldosterone system (e.g., patients with severe congestive heart failure), treatment with angiotensin converting enzyme inhibitors and angiotensin receptor antagonists has been associated with oliguria or progressive azotemia and (rarely) with acute renal failure and/or death. Similar effects may occur in patients treated with amlodipine besylate and olmesartan medoxomil because of the olmesartan medoxomil component [see Drug Interactions (7) and Clinical Pharmacology (12.3)].

In studies of ACE inhibitors in patients with unilateral or bilateral renal artery stenosis, increases in serum creatinine or blood urea nitrogen (BUN) have been reported. There has been no long-term use of olmesartan medoxomil in patients with unilateral or bilateral renal artery stenosis, but similar effects would be expected with olmesartan medoxomil and amlodipine besylate and olmesartan medoxomil.

5.5 Patients with Hepatic Impairment

Patients with hepatic impairment have decreased clearance of amlodipine. Starting amlodipine or adding amlodipine at 2.5 mg in hepatically impaired patients is recommended. The lowest dose of amlodipine besylate and olmesartan medoxomil is 5/20 mg; therefore, initial therapy with amlodipine besylate and olmesartan medoxomil is not recommended in hepatically impaired patients [see Use in Specific Populations (8.6)].

Since amlodipine is extensively metabolized by the liver and the plasma elimination half-life (t½) is 56 hours in patients with severely impaired hepatic function, titrate slowly when administering to patients with severe hepatic impairment.

5.6 Sprue-like Enteropathy

Severe, chronic diarrhea with substantial weight loss has been reported in patients taking olmesartan months to years after drug initiation. Intestinal biopsies of patients often demonstrated villous atrophy. If a patient develops these symptoms during treatment with olmesartan, exclude other etiologies. Consider discontinuation of amlodipine besylate and olmesartan medoxomil in cases where no other etiology is identified.

5.7 Electrolyte Imbalances

Amlodipine besylate and olmesartan medoxomil contains olmesartan, a drug that inhibits the renin-angiotensin system (RAS). Drugs that inhibit the RAS can cause hyperkalemia. Monitor serum electrolytes periodically.

6 ADVERSE REACTIONS

6.1 Clinical Trials Experience

Because clinical studies are conducted under widely varying conditions, adverse reaction rates observed in the clinical studies of a drug cannot be directly compared to rates in the clinical studies of another drug and may not reflect the rates observed in practice.

Amlodipine besylate and olmesartan medoxomil

The data described below reflect exposure to amlodipine besylate and olmesartan medoxomil in more than 1600 patients including more than 1000 exposed for at least 6 months and more than 700 exposed for 1 year. Amlodipine besylate and olmesartan medoxomil was studied in one placebo-controlled factorial trial [see Clinical Trials (14.1)]. The population had a mean age of 54 years and included approximately 55% males. Seventy-one percent were Caucasian and 25% were Black. Patients received doses ranging from 5/20 mg to 10/40 mg orally once daily.

The overall incidence of adverse reactions on therapy with amlodipine besylate and olmesartan medoxomil was similar to that seen with corresponding doses of the individual components of amlodipine besylate and olmesartan medoxomil, and to placebo. The reported adverse reactions were generally mild and seldom led to discontinuation of treatment (2.6% for amlodipine besylate and olmesartan medoxomil and 6.8% for placebo).

Edema

Edema is a known, dose-dependent adverse effect of amlodipine but not of olmesartan medoxomil.

The placebo-subtracted incidence of edema during the 8-week, randomized, double-blind treatment period was highest with amlodipine 10 mg monotherapy. The incidence was significantly reduced when 20 mg or 40 mg of olmesartan medoxomil was added to the 10 mg amlodipine dose.

Placebo-Subtracted Incidence of Edema During the Double-Blind Treatment Period

 |  | Olmesartan Medoxomil
 |  | Placebo | 20 mg | 40 mg
Amlodipine | Placebo | －* | -2.4% | 6.2%
 | 5 mg | 0.7% | 5.7% | 6.2%
 | 10 mg | 24.5% | 13.3% | 11.2%
*12.3% = actual placebo incidence

Across all treatment groups, the frequency of edema was generally higher in women than men, as has been observed in previous studies of amlodipine.

There was a greater decrease in hemoglobin and hematocrit in patients treated with amlodipine besylate and olmesartan medoxomil as compared to patients receiving either component.

Adverse reactions seen at lower rates during the double-blind period also occurred in the patients treated with amlodipine besylate and olmesartan medoxomil at about the same or greater incidence as in patients receiving placebo. These included hypotension, orthostatic hypotension, rash, pruritus, palpitation, urinary frequency, and nocturia.

The adverse event profile obtained from 44 weeks of open-label combination therapy with amlodipine plus olmesartan medoxomil was similar to that observed during the 8-week, double-blind, placebo-controlled period.

Initial Therapy

Analyzing the data described above specifically for initial therapy, it was observed that higher doses of amlodipine besylate and olmesartan medoxomil caused slightly more hypotension and orthostatic symptoms, but not at the recommended starting dose of amlodipine besylate and olmesartan medoxomil 5/20 mg. No increase in the incidence of syncope or near syncope was observed. The incidences of discontinuation because of any treatment emergent adverse events in the double-blind phase are summarized in the table below.

Discontinuation for any Treatment Emergent Adverse Event^1

 |  |  | Olmesartan Medoxomil
 |  | Placebo | 10 mg | 20 mg | 40 mg
Amlodipine | Placebo | 4.9% | 4.3% | 5.6% | 3.1%
 | 5 mg | 3.7% | 0.0% | 1.2% | 3.7%
 | 10 mg | 5.5% | 6.8% | 2.5% | 5.6%
^1Hypertension is counted as treatment failure and not as treatment emergent adverse event.
N=160-163 subjects per treatment group.

Amlodipine.

Amlodipine has been evaluated for safety in more than 11,000 patients in U.S. and foreign clinical trials. Most adverse reactions reported during therapy with amlodipine were of mild or moderate severity. In controlled clinical trials directly comparing amlodipine (N=1730) in doses up to 10 mg to placebo (N=1250), discontinuation of amlodipine due to adverse reactions was required in only about 1.5% of amlodipine-treated patients and about 1% of placebo-treated patients. The most common side effects were headache and edema. The incidence (%) of dose-related side effects was as follows:

Adverse Event | Placebo N=520 | 2.5 mg N=275 | 5.0 mg N=296 | 10.0 mg N=268
Edema | 0.6 | 1.8 | 3.0 | 10.8
Dizziness | 1.5 | 1.1 | 3.4 | 3.4
Flushing | 0.0 | 0.7 | 1.4 | 2.6
Palpitation | 0.6 | 0.7 | 1.4 | 4.5

For several adverse experiences that appear to be drug- and dose-related, there was a greater incidence in women than men associated with amlodipine treatment as shown in the following table:

Adverse Event | Placebo |  | Amlodipine
 | Male=% (N=914) | Female=% (N=336) | Male=% (N=1218) | Female=% (N=512)
Edema | 1.4 | 5.1 | 5.6 | 14.6
Flushing | 0.3 | 0.9 | 1.5 | 4.5
Palpitation | 0.9 | 0.9 | 1.4 | 3.3
Somnolence | 0.8 | 0.3 | 1.3 | 1.6

Olmesartan medoxomil.

Olmesartan medoxomil has been evaluated for safety in more than 3825 patients/subjects, including more than 3275 patients treated for hypertension in controlled trials. This experience included about 900 patients treated for at least 6 months and more than 525 treated for at least 1 year. Treatment with olmesartan medoxomil was well tolerated, with an incidence of adverse events similar to that seen with placebo. Events were generally mild, transient, and without relationship to the dose of olmesartan medoxomil.

The overall frequency of adverse events was not dose related. Analysis of gender, age, and race groups demonstrated no differences between olmesartan medoxomil- and placebo-treated patients. The rate of withdrawals due to adverse events in all trials of hypertensive patients was 2.4% (i.e., 79/3278) of patients treated with olmesartan medoxomil and 2.7% (i.e., 32/1179) of control patients. In placebo-controlled trials, the only adverse event that occurred in more than 1% of patients treated with olmesartan medoxomil and at a higher incidence in olmesartan medoxomil treated patients vs. placebo was dizziness (3% vs 1%).

6.2 Post-Marketing Experience

The following adverse reactions have been identified during post-approval use of the individual components of amlodipine besylate and olmesartan medoxomil. Because these reactions are reported voluntarily from a population of uncertain size, it is not always possible to reliably estimate their frequency or establish a causal relationship to drug exposure.

Amlodipine.The following post-marketing event has been reported infrequently where a causal relationship is uncertain: gynecomastia. In post-marketing experience, jaundice and hepatic enzyme elevations (mostly consistent with cholestasis or hepatitis), in some cases severe enough to require hospitalization, have been reported in association with use of amlodipine. Postmarketing reporting has also revealed a possible association between extrapyramidal disorder and amlodipine.

Olmesartan medoxomil.The following adverse reactions have been reported in post-marketing experience:

Body as a Whole:asthenia, angioedema, anaphylactic reactions, peripheral edema

Gastrointestinal:vomiting, diarrhea, sprue-like enteropathy [see Warnings and Precautions (5.6)]

Metabolic and Nutritional Disorders:hyperkalemia

Musculoskeletal:rhabdomyolysis

Urogenital System:acute renal failure, increased blood creatinine levels

Skin and Appendages:alopecia, pruritus, urticaria

Data from one controlled trial and an epidemiologic study have suggested that high-dose olmesartan may increase cardiovascular (CV) risk in diabetic patients, but the overall data are not conclusive. The randomized, placebo-controlled, double-blind ROADMAP trial (Randomized Olmesartan And Diabetes MicroAlbuminuria Prevention trial, n=4447) examined the use of olmesartan, 40 mg daily, vs. placebo in patients with type 2 diabetes mellitus, normoalbuminuria, and at least one additional risk factor for CV disease. The trial met its primary endpoint, delayed onset of microalbuminuria, but olmesartan had no beneficial effect on decline in glomerular filtration rate (GFR). There was a finding of increased CV mortality (adjudicated sudden cardiac death, fatal myocardial infarction, fatal stroke, revascularization death) in the olmesartan group compared to the placebo group (15 olmesartan vs. 3 placebo, HR 4.9, 95% confidence interval [CI], 1.4, 17), but the risk of nonfatal myocardial infarction was lower with olmesartan (HR 0.64, 95% CI 0.35, 1.18).

The epidemiologic study included patients 65 years and older with overall exposure of > 300,000 patient-years. In the sub-group of diabetic patients receiving high-dose olmesartan (40 mg/d) for > 6 months, there appeared to be an increased risk of death (HR 2.0, 95% CI 1.1, 3.8) compared to similar patients taking other angiotensin receptor blockers. In contrast, high-dose olmesartan use in non-diabetic patients appeared to be associated with a decreased risk of death (HR 0.46, 95% CI 0.24, 0.86) compared to similar patients taking other angiotensin receptor blockers. No differences were observed between the groups receiving lower doses of olmesartan compared to other angiotensin blockers or those receiving therapy for < 6 months.

Overall, these data raise a concern of a possible increased CV risk associated with the use of high-dose olmesartan in diabetic patients. There are, however, concerns with the credibility of the finding of increased CV risk, notably the observation in the large epidemiologic study for a survival benefit in non-diabetics of a magnitude similar to the adverse finding in diabetics.

7 DRUG INTERACTIONS

7.1 Drug Interactions with Amlodipine

Simvastatin: Co-administration of simvastatin with amlodipine increases the systemic exposure of simvastatin. Limit the dose of simvastatin in patients on amlodipine to 20 mg daily [see Clinical Pharmacology (12.3)].

Immunosuppressants:Amlodipine may increase the systemic exposure of cyclosporine or tacrolimus when co-administered. Frequent monitoring of trough blood levels of cyclosporine and tacrolimus is recommended and adjust the dose when appropriate [see Clinical Pharmacology (12.3)].

CYP3A Inhibitors:Co-administration of amlodipine with CYP3A inhibitors (moderate and strong) results in increased systemic exposure to amlodipine and may require dose reduction. Monitor for symptoms of hypotension and edema when amlodipine is co-administered with CYP3A inhibitors to determine the need for dose adjustment .

CYP3A Inducers:No information is available on the quantitative effects of CYP3A inducers on amlodipine. Blood pressure should be closely monitored when amlodipine is co-administered with CYP3A inducers.

7.2 Drug Interactions with Olmesartan Medoxomil

Non-Steroidal Anti-Inflammatory Agents including Selective Cyclooxygenase-2 Inhibitors (COX-2 Inhibitors):

In patients who are elderly, volume-depleted (including those on diuretic therapy), or with compromised renal function, co-administration of NSAIDs, including selective COX-2 inhibitors, with angiotensin II receptor antagonists, including olmesartan medoxomil, may result in deterioration of renal function, including possible acute renal failure. These effects are usually reversible. Monitor renal function periodically in patients receiving olmesartan medoxomil and NSAID therapy.

The antihypertensive effect of angiotensin II receptor antagonists, including olmesartan medoxomil may be attenuated by NSAIDs including selective COX-2 inhibitors.

Dual Blockade of the Renin-Angiotensin System (RAS):

Dual blockade of the RAS with angiotensin receptor blockers, ACE inhibitors, or aliskiren is associated with increased risks of hypotension, hyperkalemia, and changes in renal function (including acute renal failure) compared to monotherapy. Most patients receiving the combination of two RAS inhibitors do not obtain any additional benefit compared to monotherapy. In general, avoid combined use of RAS inhibitors. Closely monitor blood pressure, renal function and electrolytes in patients on amlodipine besylate and olmesartan medoxomil and other agents that affect the RAS.

Do not co-administer aliskiren with amlodipine besylate and olmesartan medoxomil in patients with diabetes [see Contraindications (4)]. Avoid use of aliskiren with amlodipine besylate and olmesartan medoxomil in patients with renal impairment (GFR <60 ml/min).

Use with Colesevelam Hydrochloride:

Concurrent administration of bile acid sequestering agent colesevelam hydrochloride reduces the systemic exposure and peak plasma concentration of olmesartan. Administration of olmesartan at least 4 hours prior to colesevelam hydrochloride decreased the drug interaction effect. Consider administering olmesartan at least 4 hours before the colesevelam hydrochloride dose [see Clinical Pharmacology (12.3)].

Lithium:

Increases in serum lithium concentrations and lithium toxicity have been reported during concomitant administration of lithium with angiotensin II receptor antagonists, including amlodipine besylate and olmesartan medoxomil. Monitor serum lithium levels during concomitant use.

8 USE IN SPECIFIC POPULATIONS

8.1 Pregnancy

Risk Summary

Amlodipine besylate and olmesartan medoxomil can cause fetal harm when administered to a pregnant woman. Use of drugs that act on the renin-angiotensin system during the second and third trimesters of pregnancy reduces fetal renal function and increases fetal and neonatal morbidity and death [see Clinical Considerations]. Most epidemiologic studies examining fetal abnormalities after exposure to antihypertensive use in the first trimester have not distinguished drugs affecting the renin-angiotensin system from other antihypertensive agents.

When pregnancy is detected, discontinue amlodipine besylate and olmesartan medoxomil as soon as possible. Consider alternative antihypertensive therapy during pregnancy.

The estimated background risk of major birth defects and miscarriage for the indicated population is unknown. All pregnancies have a background risk of birth defect, loss or other adverse outcomes. In the U.S. general population, the estimated background risk of major birth defects and miscarriage in clinically recognized pregnancies is 2%–4% and 15%–20%, respectively.

Clinical Considerations

Disease-Associated Maternal and/or Embryo/Fetal Risk

Hypertension in pregnancy increases the maternal risk for pre-eclampsia, gestational diabetes, premature delivery, and delivery complications (e.g., need for cesarean section and post-partum hemorrhage). Hypertension increases the fetal risk for intrauterine growth restriction and intrauterine death. Pregnant women with hypertension should be carefully monitored and managed accordingly.

Fetal/Neonatal Adverse Reactions

Olmesartan medoxomil

Oligohydramnios in pregnant women who use drugs affecting the renin-angiotensin system in the second and third trimesters of pregnancy can result in the following: reduced fetal renal function leading to anuria and renal failure, fetal lung hypoplasia, skeletal deformations, including skull hypoplasia, hypotension, and death.

Perform serial ultrasound examinations to assess the intra-amniotic environment. Fetal testing may be appropriate, based on the week of gestation. Patients and physicians should be aware, however, that oligohydramnios may not appear until after the fetus has sustained irreversible injury.

Closely observe infants with histories of in uteroexposure to olmesartan for hypotension, oliguria, and hyperkalemia. In neonates with a history of in uteroexposure to olmesartan, if oliguria or hypotension occur, utilize measures to maintain adequate blood pressure and renal perfusion. Exchange transfusions or dialysis may be required as a means of reversing hypotension and supporting renal function [see Use in Specific Populations (8.4)].

Data

Animal Data

No reproductive studies have been conducted with the combination of olmesartan medoxomil, and amlodipine. However, these studies have been conducted for olmesartan medoxomil and amlodipine alone.

Olmesartan medoxomil

No teratogenic effects were observed when olmesartan medoxomil was administered to pregnant rats at oral doses up to 1000 mg/kg/day (240 times the maximum recommended human dose [MRHD] on a mg/m^2basis) or pregnant rabbits at oral doses up to 1 mg/kg/day (half the MRHD on a mg/m^2basis; higher doses could not be evaluated for effects on fetal development as they were lethal to the does). In rats, significant decreases in pup birth weight and weight gain were observed at doses ≥1.6 mg/kg/day, and delays in developmental milestones (delayed separation of ear auricular, eruption of lower incisors, appearance of abdominal hair, descent of testes, and separation of eyelids) and dose-dependent increases in the incidence of dilation of the renal pelvis were observed at doses ≥ 8 mg/kg/day. The no observed effect dose for developmental toxicity in rats is 0.3 mg/kg/day, about one-tenth the MRHD of 40 mg/day.

Amlodipine

No evidence of teratogenicity or other embryo/fetal toxicity was found when pregnant rats and rabbits were treated orally with amlodipine maleate at doses of up to 10 mg amlodipine/kg/day (respectively about 10 and 20 times the maximum recommended human dose of 10 mg amlodipine on a mg/m^2basis) during their respective periods of major organogenesis (calculations based on a patient weight of 60 kg). However, litter size was significantly decreased (by about 50%), and the number of intrauterine deaths was significantly increased (about 5-fold) in rats receiving amlodipine maleate at a dose equivalent to 10 mg amlodipine/kg/day for 14 days before mating and throughout mating and gestation. Amlodipine maleate has been shown to prolong both the gestational period and the duration of labor in rats at this dose.

8.2 Lactation

Risk Summary

There is limited information regarding the presence of amlodipine besylate and olmesartan medoxomil in human milk, the effects on the breastfed infant, or the effects on milk production. Amlodipine is present in human milk. Olmesartan is present in rat milk [see Data] . Because of the potential for adverse effects on the nursing infant, advise a nursing woman that breastfeeding is not recommended during treatment with amlodipine besylate and olmesartan medoxomil.

Data

Presence of olmesartan in milk was observed after a single oral administration of 5 mg/kg [^14C] olmesartan medoxomil to lactating rats.

8.4 Pediatric Use

The safety and effectiveness of amlodipine besylate and olmesartan medoxomil in pediatric patients have not been established.

8.5 Geriatric Use

Of the total number of subjects in the double-blind clinical study of amlodipine besylate and olmesartan medoxomil, 20% (384/1940) were 65 years of age or older and 3% (62/1940) were 75 years or older. No overall differences in safety or effectiveness were observed between subjects 65 years of age or older and younger subjects.

Elderly patients have decreased clearance of amlodipine. Starting amlodipine or adding amlodipine at 2.5 mg in patients ≥75 years old is recommended. The lowest dose of amlodipine besylate and olmesartan medoxomil is 5/20 mg; therefore, initial therapy with amlodipine besylate and olmesartan medoxomil is not recommended in patients ≥75 years old.

Amlodipine.Reported clinical experience has not identified differences in responses between the elderly and younger patients. In general, dose selection for an elderly patient should be cautious, usually starting at the low end of the dosing range, reflecting the greater frequency of decreased hepatic, renal, or cardiac function, and of concomitant disease or other drug therapy. Elderly patients have decreased clearance of amlodipine with a resulting increase of AUC of approximately 40% to 60%, and a lower initial dose may be required.

Olmesartan medoxomil.Of the total number of hypertensive patients receiving olmesartan medoxomil in clinical studies, more than 20% were 65 years of age and over, while more than 5% were 75 years of age and older. No overall differences in effectiveness or safety were observed between elderly patients and younger patients. Other reported clinical experience has not identified differences in responses between the elderly and younger patients, but greater sensitivity of some older individuals cannot be ruled out.

8.6 Hepatic Impairment

There are no studies of amlodipine besylate and olmesartan medoxomil in patients with hepatic insufficiency, but both amlodipine and olmesartan medoxomil show moderate increases in exposure in patients with hepatic impairment.

The recommended initial dose of amlodipine in patients with severe hepatic impairment is 2.5 mg, a dose not available with amlodipine besylate and olmesartan medoxomil.

Amlodipine.Amlodipine is extensively metabolized by the liver and the plasma elimination half-life (t½) is 56 hours in patients with severely impaired hepatic function [see Warnings and Precautions (5.5)].

Olmesartan medoxomil. Increases in AUC0-∞ and peak plasma concentration (Cmax) for olmesartan were observed with moderate hepatic impairment compared to those in matched controls with an increase in AUC of about 60%.

8.7 Renal Impairment

There are no studies of amlodipine besylate and olmesartan medoxomil in patients with renal impairment.

Amlodipine.The pharmacokinetics of amlodipine are not significantly influenced by renal impairment. Patients with renal failure may therefore receive the usual initial dose.

Olmesartan medoxomil.Patients with renal insufficiency have elevated serum concentrations of olmesartan compared with patients with normal renal function. After repeated dosing, AUC was approximately tripled in patients with severe renal impairment (creatinine clearance <20 mL/min). No initial dosage adjustment is recommended for patients with moderate to marked renal impairment (creatinine clearance <40 mL/min).

8.8 Black Patients

Of the total number of subjects in the double-blind clinical study of amlodipine besylate and olmesartan medoxomil, 25% (481/1940) were black patients. Amlodipine besylate and olmesartan medoxomil was effective in treating black patients (usually a low-renin population), and the magnitude of blood pressure reduction in black patients approached that observed for non-black patients.

10 OVERDOSAGE

There is no information on overdosage with amlodipine besylate and olmesartan medoxomil in humans.

Amlodipine.Single oral doses of amlodipine maleate equivalent to 40 mg amlodipine/kg and 100 mg amlodipine/kg in mice and rats, respectively, caused deaths. Single oral amlodipine maleate doses equivalent to 4 or more mg amlodipine/kg or higher in dogs (11 or more times the maximum recommended human dose on a mg/m^2basis) caused a marked peripheral vasodilation and hypotension.

Overdosage might be expected to cause excessive peripheral vasodilation with marked hypotension and possibly a reflex tachycardia. In humans, experience with intentional overdosage of amlodipine is limited.

If massive overdose should occur, active cardiac and respiratory monitoring should be instituted. Frequent blood pressure measurements are essential. Should hypotension occur, cardiovascular support including elevation of the extremities and the judicious administration of fluids should be initiated. If hypotension remains unresponsive to these conservative measures, administration of vasopressors (such as phenylephrine) should be considered with attention to circulating volume and urine output. Intravenous calcium gluconate may help to reverse the effects of calcium entry blockade. As amlodipine is highly protein bound, hemodialysis is not likely to be of benefit.

Olmesartan medoxomil.Limited data are available related to overdosage in humans. The most likely manifestations of overdosage would be hypotension and tachycardia; bradycardia could be encountered if parasympathetic (vagal) stimulation occurs. If symptomatic hypotension should occur, supportive treatment should be initiated. The dialyzability of olmesartan is unknown.

11 DESCRIPTION

Amlodipine besylate and olmesartan medoxomil provided as a tablet for oral administration, is a combination of the calcium channel blocker (CCB) amlodipine besylate and the angiotensin II receptor blocker (ARB) olmesartan medoxomil.

The amlodipine besylate component of amlodipine besylate and olmesartan medoxomil is chemically described as 3-ethyl-5-methyl (±)-2-[(2-aminoethoxy)methyl]-4-(2-chlorophenyl)-1,4-dihydro-6-methyl-3,5-pyridinedicarboxylate, monobenzenesulphonate. Its empirical formula is C20H25ClN2O5•C6H6O3S.

Olmesartan medoxomil, a prodrug, is hydrolyzed to olmesartan during absorption from the gastrointestinal tract.

The olmesartan medoxomil component of amlodipine besylate and olmesartan medoxomil is chemically described as 2,3-dihydroxy-2-butenyl 4-(1-hydroxy-1-methylethyl)-2-propyl-1-[ p-(o-1 H-tetrazol-5-ylphenyl)benzyl]imidazole-5-carboxylate, cyclic 2,3-carbonate. Its empirical formula is C29H30N6O6.

The structural formula for amlodipine besylate is:

The structural formula for olmesartan medoxomil is:

Amlodipine besylate and olmesartan medoxomil contains amlodipine besylate, a white to off-white crystalline powder, and olmesartan medoxomil, a white to light yellowish-white powder or crystalline powder. The molecular weights of amlodipine besylate and olmesartan medoxomil are 567.1 and 558.59, respectively. Amlodipine besylate is slightly soluble in water and sparingly soluble in ethanol. Olmesartan medoxomil is practically insoluble in water and sparingly soluble in methanol.

Each tablet of amlodipine besylate and olmesartan medoxomil also contains the following inactive ingredients: silicified microcrystalline cellulose, pregelatinized starch, croscarmellose sodium, and magnesium stearate. The color coatings contain polyvinyl alcohol, macrogol/ polyethylene glycol 3350, titanium dioxide, talc, iron oxide yellow (5/40 mg, 10/20 mg, 10/40 mg tablets), iron oxide red (10/20 mg and 10/40 mg tablets), and iron oxide black (10/20 mg tablets).

12 CLINICAL PHARMACOLOGY

12.1 Mechanism of Action

Amlodipine besylate and olmesartan medoxomil is a combination of two antihypertensive drugs: a dihydropyridine calcium antagonist (calcium ion antagonist or slow-channel blocker), amlodipine besylate, and an angiotensin II receptor blocker, olmesartan medoxomil. The amlodipine component of amlodipine besylate and olmesartan medoxomil inhibits the transmembrane influx of calcium ions into vascular smooth muscle and cardiac muscle, and the olmesartan medoxomil component of amlodipine besylate and olmesartan medoxomil blocks the vasoconstrictor effects of angiotensin II.

Amlodipine.Experimental data suggests that amlodipine binds to both dihydropyridine and nonhydropyridine binding sites. The contractile processes of cardiac muscle and vascular smooth muscle are dependent upon the movement of extracellular calcium ions into these cells through specific ion channels. Amlodipine inhibits calcium ion influx across cell membranes selectively, with a greater effect on vascular smooth muscle cells than on cardiac muscle cells. Negative inotropic effects can be detected invitrobut such effects have not been seen in intact animals at therapeutic doses. Serum calcium concentration is not affected by amlodipine. Within the physiologic pH range, amlodipine is an ionized compound (pKa=8.6), and its kinetic interaction with the calcium channel receptor is characterized by a gradual rate of association and dissociation with the receptor binding site, resulting in a gradual onset of effect.

Amlodipine is a peripheral arterial vasodilator that acts directly on vascular smooth muscle to cause a reduction in peripheral vascular resistance and reduction in blood pressure.

Olmesartan medoxomil.Angiotensin II is formed from angiotensin I in a reaction catalyzed by angiotensin converting enzyme (ACE, kininase II). Angiotensin II is the principal pressor agent of the renin-angiotensin system, with effects that include vasoconstriction, stimulation of synthesis and release of aldosterone, cardiac stimulation and renal reabsorption of sodium. Olmesartan blocks the vasoconstrictor effects of angiotensin II by selectively blocking the binding of angiotensin II to the AT1receptor in vascular smooth muscle. Its action is, therefore, independent of the pathways for angiotensin II synthesis.

An AT2receptor is found also in many tissues, but this receptor is not known to be associated with cardiovascular homeostasis. Olmesartan has more than a 12,500-fold greater affinity for the AT1receptor than for the AT2receptor.

Blockade of the renin-angiotensin system with ACE inhibitors, which inhibit the biosynthesis of angiotensin II from angiotensin I, is a mechanism of many drugs used to treat hypertension. ACE inhibitors also inhibit the degradation of bradykinin, a reaction also catalyzed by ACE. Because olmesartan does not inhibit ACE (kininase II), it does not affect the response to bradykinin. Whether this difference has clinical relevance is not yet known.

Blockade of the angiotensin II receptor inhibits the negative regulatory feedback of angiotensin II on renin secretion, but the resulting increased plasma renin activity and circulating angiotensin II levels do not overcome the effect of olmesartan on blood pressure.

12.2 Pharmacodynamics

Amlodipine.Following administration of therapeutic doses to patients with hypertension, amlodipine produces vasodilation resulting in a reduction of supine and standing blood pressures. These decreases in blood pressure are not accompanied by a significant change in heart rate or plasma catecholamine levels with chronic dosing.

With chronic once daily oral administration, antihypertensive effectiveness is maintained for at least 24 hours. Plasma concentrations correlate with effect in both young and elderly patients. The magnitude of reduction in blood pressure with amlodipine is also correlated with the height of pretreatment elevation; thus, individuals with moderate hypertension (diastolic pressure 105-114 mmHg) had about a 50% greater response than patients with mild hypertension (diastolic pressure 90-104 mmHg). Normotensive subjects experienced no clinically significant change in blood pressures (+1/-2 mmHg).In hypertensive patients with normal renal function, therapeutic doses of amlodipine resulted in a decrease in renal vascular resistance and an increase in glomerular filtration rate and effective renal plasma flow without change in filtration fraction or proteinuria.

As with other calcium channel blockers, hemodynamic measurements of cardiac function at rest and during exercise (or pacing) in patients with normal ventricular function treated with amlodipine have generally demonstrated a small increase in cardiac index without significant influence on dP/dt or on left ventricular end diastolic pressure or volume. In hemodynamic studies, amlodipine has not been associated with a negative inotropic effect when administered in the therapeutic dose range to intact animals and man, even when co-administered with beta-blockers to man. Similar findings, however, have been observed in normals or well-compensated patients with heart failure with agents possessing significant negative inotropic effects.

Amlodipine does not change sinoatrial nodal function or atrioventricular conduction in intact animals or man. In clinical studies in which amlodipine was administered in combination with beta-blockers to patients with either hypertension or angina, no adverse effects on electrocardiographic parameters were observed.

Olmesartan medoxomil.Olmesartan medoxomil doses of 2.5 mg to 40 mg inhibit the pressor effects of angiotensin I infusion. The duration of the inhibitory effect was related to dose, with doses of olmesartan medoxomil >40 mg giving >90% inhibition at 24 hours.

Plasma concentrations of angiotensin I and angiotensin II and plasma renin activity (PRA) increase after single and repeated administration of olmesartan medoxomil to healthy subjects and hypertensive patients. Repeated administration of up to 80 mg olmesartan medoxomil had minimal influence on aldosterone levels and no effect on serum potassium.

12.3 Pharmacokinetics

The pharmacokinetics of amlodipine and olmesartan medoxomil from amlodipine besylate and olmesartan medoxomil are equivalent to the pharmacokinetics of amlodipine and olmesartan medoxomil when administered separately. The bioavailability of both components is well below 100%, but neither component is affected by food. The effective half-lives of amlodipine (45±11 hours) and olmesartan (7±1 hours) result in a 2- to 3- fold accumulation for amlodipine and negligible accumulation for olmesartan with once-daily dosing.

Amlodipine.After oral administration of therapeutic doses of amlodipine, absorption produces peak plasma concentrations between 6 and 12 hours. Absolute bioavailability is estimated as between 64% and 90%.

Olmesartan medoxomil.Olmesartan medoxomil is rapidly and completely bioactivated by ester hydrolysis to olmesartan during absorption from the gastrointestinal tract. The absolute bioavailability of olmesartan medoxomil is approximately 26%. After oral administration, the peak plasma concentration (Cmax) of olmesartan is reached after 1 to 2 hours. Food does not affect the bioavailability of olmesartan medoxomil.

Distribution

Amlodipine. Ex vivostudies have shown that approximately 93% of the circulating drug is bound to plasma proteins in hypertensive patients. Steady-state plasma levels of amlodipine are reached after 7 to 8 days of consecutive daily dosing.

Olmesartan medoxomil.The volume of distribution of olmesartan is approximately 17 L. Olmesartan is highly bound to plasma proteins (99%) and does not penetrate red blood cells. The protein binding is constant at plasma olmesartan concentrations well above the range achieved with recommended doses.

In rats, olmesartan crossed the blood-brain barrier poorly, if at all. Olmesartan passed across the placental barrier in rats and was distributed to the fetus. Olmesartan was distributed to milk at low levels in rats.

Metabolism and Excretion

Amlodipine.Amlodipine is extensively (about 90%) converted to inactive metabolites via hepatic metabolism. Elimination from the plasma is biphasic with a terminal elimination half-life of about 30 to 50 hours. Ten percent of the parent compound and 60% of the metabolites are excreted in the urine.

Olmesartan medoxomil.Following the rapid and complete conversion of olmesartan medoxomil to olmesartan during absorption, there is virtually no further metabolism of olmesartan.Total plasma clearance of olmesartan is 1.3 L/h, with a renal clearance of 0.6 L/h. Approximately 35% to 50% of the absorbed dose is recovered in urine while the remainder is eliminated in feces via the bile.

Olmesartan appears to be eliminated in a biphasic manner with a terminal elimination half-life of approximately 13 hours. Olmesartan shows linear pharmacokinetics following single oral doses of up to 320 mg and multiple oral doses of up to 80 mg. Steady-state levels of olmesartan are achieved within 3 to 5 days and no accumulation in plasma occurs with once-daily dosing.

Specific Populations

Geriatric Patients

The pharmacokinetic properties of amlodipine besylate and olmesartan medoxomil in the elderly are similar to those of the individual components.

Amlodipine.Elderly patients have decreased clearance of amlodipine with a resulting increase in AUC of approximately 40% to 60%, and a lower initial dose may be required.

Olmesartan medoxomil.The pharmacokinetics of olmesartan medoxomil were studied in the elderly (≥65 years). Overall, maximum plasma concentrations of olmesartan were similar in young adults and the elderly. Modest accumulation of olmesartan was observed in the elderly with repeated dosing; AUCѕѕ,τwas 33% higher in elderly patients, corresponding to an approximate 30% reduction in CLR.

Pediatric Patients

Amlodipine.Sixty-two hypertensive patients aged 6 to 17 years received doses of amlodipine between 1.25 mg and 20 mg. Weight-adjusted clearance and volume of distribution were similar to values in adults.

Olmesartan medoxomil.The pharmacokinetics of olmesartan medoxomil have not been investigated in patients <18 years of age.

Male and Female Patients

Population pharmacokinetic analysis indicated that female patients had approximately 15% smaller clearances of olmesartan than male patients. Gender had no effect on the clearance of amlodipine.

Olmesartan medoxomil.Minor differences were observed in the pharmacokinetics of olmesartan medoxomil in women compared to men. AUC and Cmaxwere 10% to 15% higher in women than in men.

Patients with Renal Impairment

Amlodipine.The pharmacokinetics of amlodipine are not significantly influenced by renal impairment. Patients with renal failure may therefore receive the usual initial dose.

Olmesartan medoxomil.In patients with renal insufficiency, serum concentrations of olmesartan were elevated compared to subjects with normal renal function. After repeated dosing, the AUC was approximately tripled in patients with severe renal impairment (creatinine clearance <20 mL/min). The pharmacokinetics of olmesartan medoxomil in patients undergoing hemodialysis has not been studied. No initial dosage adjustment is recommended for patients with moderate to marked renal impairment (creatinine clearance <40 mL/min).

Patients with Hepatic Impairment

Amlodipine.Patients with hepatic insufficiency have decreased clearance of amlodipine with a resulting increase in AUC of approximately 40% to 60%.

Olmesartan medoxomil.Increases in AUC0-∞and Cmaxwere observed in patients with moderate hepatic impairment compared to those in matched controls, with an increase in AUC of about 60%.

Heart Failure

Amlodipine.Patients with heart failure have decreased clearance of amlodipine with a resulting increase in AUC of approximately 40% to 60%.

Drug Interaction Studies

Simvastatin: Co-administration of multiple doses of 10 mg of amlodipine with 80 mg simvastatin resulted in a 77% increase in exposure to simvastatin compared to simvastatin alone. [see Drug Interactions (7.1)].

CYP3A inhibitors: Co-administration of a 180 mg daily dose of diltiazem with 5 mg amlodipine in elderly hypertensive patients resulted in a 60% increase in amlodipine systemic exposure. Erythromycin co-administration in healthy volunteers did not significantly change amlodipine systemic exposure. However, strong inhibitors of CYP3A (e.g., itraconazole, clarithromycin) may increase the plasma concentrations of amlodipine to a greater extent [see Drug Interactions (7.1)].

Cyclosporine:In a prospective study in renal transplant patients, an average 40% increase in trough cyclosporine levels was observed in the presence of amlodipine. [see Drug Interactions (7.1)].

Colesevelam: Concomitant administration of 40 mg olmesartan medoxomil and 3750 mg colesevelam hydrochloride in healthy subjects resulted in 28% reduction in Cmax and 39% reduction in AUC of olmesartan. Lesser effects, 4% and 15% reduction in Cmax and AUC respectively, were observed when olmesartan medoxomil was administered 4 hours prior to colesevelam hydrochloride [see Drug Interactions (7.2)].

Cimetidine:Co-administration of amlodipine with cimetidine did not alter the pharmacokinetics of amlodipine.

Grapefruit juice:Co-administration of 240 mL of grapefruit juice with a single oral dose of amlodipine 10 mg in 20 healthy volunteers had no significant effect on the pharmacokinetics of amlodipine.

Maalox® (antacid):Co-administration of the antacid Maalox ®with a single dose of amlodipine had no significant effect on the pharmacokinetics of amlodipine.

Sildenafil:A single 100 mg dose of sildenafil in subjects with essential hypertension had no effect on the pharmacokinetic parameters of amlodipine. When amlodipine and sildenafil were used in combination, each agent independently exerted its own blood pressure lowering effect.

Atorvastatin:Co-administration of multiple 10 mg doses of amlodipine with 80 mg of atorvastatin resulted in no significant change in the steady state pharmacokinetic parameters of atorvastatin.

Digoxin:Co-administration of amlodipine with digoxin did not change serum digoxin levels or digoxin renal clearance in normal volunteers.

No significant drug interactions were reported in studies in which olmesartan medoxomil was coadministered with digoxin in healthy volunteers.

Ethanol (alcohol):Single and multiple 10 mg doses of amlodipine had no significant effect on the pharmacokinetics of ethanol.

Warfarin:Co-administration of amlodipine with warfarin did not change the warfarin prothrombin response time. No significant drug interactions were reported in studies in which olmesartan medoxomil was coadministered with warfarin in healthy volunteers.

Antacids: The bioavailability of olmesartan medoxomil was not significantly altered by the co-administration of antacids [Al(OH)3/Mg(OH)2].

13 NONCLINICAL TOXICOLOGY

13.1 Carcinogenesis, Mutagenesis, Impairment of Fertility

Amlodipine.Rats and mice treated with amlodipine maleate in the diet for up to two years, at concentrations calculated to provide daily dosage levels of amlodipine 0.5, 1.25, and 2.5 mg/kg/day showed no evidence of a carcinogenic effect of the drug. For the mouse, the highest dose was, on a mg/m^2basis, similar to the maximum recommended human dose (MRHD) of amlodipine 10 mg/day. For the rat, the highest dose was, on a mg/m^2basis, about two and a half times the MRHD. (Calculations based on a 60 kg patient.)

Mutagenicity studies conducted with amlodipine maleate revealed no drug related effects at either the gene or chromosome level.

There was no effect on the fertility of rats treated orally with amlodipine maleate (males for 64 days and females for 14 days prior to mating) at doses of amlodipine up to 10 mg/kg/day (about 10 times the MRHD of 10 mg/day on a mg/m^2basis).

Olmesartan medoxomil.Olmesartan was not carcinogenic when administered by dietary administration to rats for up to 2 years. The highest dose tested (2000 mg/kg/day) was, on a mg/m^2basis, about 480 times the maximum recommended human dose (MRHD) of 40 mg/day. Two carcinogenicity studies conducted in mice, a 6-month gavage study in the p53 knockout mouse and a 6-month dietary administration study in the Hras2 transgenic mouse, at doses of up to 1000 mg/kg/day (about 120 times the MRHD), revealed no evidence of a carcinogenic effect of olmesartan.

Both olmesartan medoxomil and olmesartan tested negative in the in vitroSyrian hamster embryo cell transformation assay and showed no evidence of genetic toxicity in the Ames (bacterial mutagenicity) test. However, both were shown to induce chromosomal aberrations in cultured cells in vitro(Chinese hamster lung) and tested positive for thymidine kinase mutations in the in vitromouse lymphoma assay. Olmesartan medoxomil tested negative in vivofor mutations in the MutaMouse intestine and kidney and for clastogenicity in mouse bone marrow (micronucleus test) at oral doses of up to 2000 mg/kg (olmesartan not tested).

Fertility of rats was unaffected by administration of olmesartan at dose levels as high as 1000 mg/kg/day (240 times the MRHD) in a study in which dosing was begun 2 (female) or 9 (male) weeks prior to mating.

14 CLINICAL STUDIES

14.1 Amlodipine Besylate and Olmesartan Medoxomil

An 8-week multicenter, randomized, double-blind, placebo controlled, parallel group factorial study in patients with mild to severe hypertension was conducted to determine if treatment with amlodipine besylate and olmesartan medoxomil was associated with clinically significant reduction in blood pressure compared to the respective monotherapies. The study randomized 1940 patients equally to one of the following 12 treatment arms: placebo, monotherapy treatment with amlodipine 5 mg or 10 mg, monotherapy treatment with olmesartan medoxomil 10 mg, 20 mg, or 40 mg, or combination therapy with amlodipine/ olmesartan medoxomil at doses of 5/10 mg, 5/20 mg, 5/40 mg, 10/10 mg, 10/20 mg, and 10/40 mg. Patients discontinued their prior antihypertensive treatment. The mean baseline blood pressure of the study population was 164/102 mmHg. Of the total cohort, 970 patients were treated with the combination as initial therapy.

Treatment with amlodipine besylate and olmesartan medoxomil resulted in statistically significant greater reductions in diastolic and systolic blood pressure compared to the respective monotherapy components. Maximum antihypertensive effects were attained within 2 weeks after a change in dose.

The following table presents the results for mean reduction in seated systolic and diastolic blood pressure following 8 weeks of treatment with amlodipine besylate and olmesartan medoxomil. Placebo-adjusted reductions from baseline in blood pressure were progressively greater with increases in dose of both amlodipine and olmesartan medoxomil components of amlodipine besylate and olmesartan medoxomil.

Reduction in Seated Systolic/Diastolic Blood Pressure (mmHg): Combination Therapy vs. Monotherapy Components (Double-Blind Treatment Period)

 |  | Olmesartan medoxomil
 |  | (mmHg) | Placebo | 10 mg | 20 mg | 40 mg
Amlodipine | Placebo | Mean Change | -5/-3 | -12/-8 | -14/-9 | -16/-10
 |  | Placebo-Adjusted Mean Change | -- | -8/-5 | -10/-6 | -13/-7
 | 5 mg | Mean Change | -15/-9 | -24/-14 | -24/-14 | -25/-16
 |  | Placebo-Adjusted Mean Change | -12/-7 | -20/-11 | -20/-11 | -22/-13
 | 10 mg | Mean Change | -20/-13 | -25/-16 | -29/-17 | -30/-19
 |  | Placebo-Adjusted Mean Change | -16/-10 | -22/-13 | -25/-14 | -26/-16

The antihypertensive effect of amlodipine besylate and olmesartan medoxomil was similar in patients with and without prior antihypertensive medication use, in patients with and without diabetes, in patients ≥65 years of age and <65 years of age, and in women and men. Limited data exist in patients ≥75 years of age.

Amlodipine besylate and olmesartan medoxomil was effective in treating black patients (usually a low-renin population), and the magnitude of blood pressure reduction in black patients approached that observed for non-Black patients. This effect in black patients has been seen with ACE inhibitors, angiotensin receptor blockers, and beta-blockers.

The blood pressure lowering effect was maintained throughout the 24-hour period with amlodipine besylate and olmesartan medoxomil once daily, with trough-to-peak ratios for systolic and diastolic response between 71% and 82%.

Upon completing the 8-week, double-blind, placebo-controlled study, 1684 patients entered a 44-week open-label extension and received combination therapy with amlodipine 5 mg plus olmesartan medoxomil 40 mg. During the open-label extension, patients whose blood pressure was not adequately controlled (i.e., did not achieve a blood pressure goal of <140/90 mmHg, or <130/80 mmHg for those patients with diabetes) on amlodipine/olmesartan medoxomil 5/40 mg were titrated to amlodipine /olmesartan medoxomil 10/40 mg. Patients whose blood pressure was still not adequately controlled were offered additional hydrochlorothiazide 12.5 mg and subsequently 25 mg as required to achieve adequate blood pressure goal.

There are no trials of amlodipine besylate and olmesartan medoxomil demonstrating reductions in cardiovascular risk in patients with hypertension, but at least one pharmacologically similar drug has demonstrated such benefits.

14.2 Amlodipine

The antihypertensive efficacy of amlodipine has been demonstrated in a total of 15 double-blind, placebo-controlled, randomized studies involving 800 patients on amlodipine and 538 on placebo. Once daily administration produced statistically significant placebo-corrected reductions in supine and standing blood pressures at 24 hours post-dose, averaging about 12/6 mmHg in the standing position and 13/7 mmHg in the supine position in patients with mild to moderate hypertension. Maintenance of the blood pressure effect over the 24-hour dosing interval was observed, with little difference in peak and trough effect.

14.3 Olmesartan Medoxomil

The antihypertensive effects of olmesartan medoxomil have been demonstrated in seven placebo-controlled studies at doses ranging from 2.5 mg to 80 mg for 6 to 12 weeks, each showing statistically significant reductions in peak and trough blood pressure. A total of 2693 patients (2145 olmesartan medoxomil; 548 placebo) with essential hypertension were studied. The blood pressure lowering effect was maintained throughout the 24-hour period with olmesartan medoxomil once daily, with trough-to-peak ratios for systolic and diastolic response between 60% and 80%.

16 HOW SUPPLIED/STORAGE AND HANDLING

Amlodipine besylate and olmesartan medoxomil tablets contain amlodipine besylate at a dose equivalent to 5 or 10 mg amlodipine and olmesartan medoxomil in the strengths described below.

Amlodipine besylate and olmesartan medoxomil tablets are differentiated by tablet color/size and are debossed with an individual product tablet code on one side. Amlodipine besylate and olmesartan medoxomil tablets are supplied for oral administration in the following strength and package configurations:

Tablet Strength (amlodipine equivalent/ olmesartan medoxomil) mg | Package Configuration | NDC# | Product Code | Tablet Color
5/20 mg | Bottle of 30 Bottle of 90 10 blisters of 10 Bottle of 1000 | 51407-857-30 Not available Not available Not available | C73 | White
10/20 mg | Bottle of 30 Bottle of 90 10 blisters of 10 Bottle of 1000 | 51407-858-30 Not available Not available Not available | C74 | Grayish; Orange
5/40 mg | Bottle of 30 Bottle of 90 10 blisters of 10 Bottle of 1000 | 51407-859-30 Not available Not available Not available | C75 | Cream
10/40 mg | Bottle of 30 Bottle of 90 10 blisters of 10 Bottle of 1000 | 51407-860-30 Not available Not available Not available | C77 | Brownish; Red

Store at 25ºC (77ºF); excursions permitted to 15ºC-30ºC (59ºF-86ºF) [see USP Controlled Room Temperature].

17 PATIENT COUNSELING INFORMATION

Pregnancy: Advise female patients of childbearing age about the consequences of exposure to amlodipine besylate and olmesartan medoxomil during pregnancy. Discuss treatment options with women planning to become pregnant. Tell patients to report pregnancies to their physicians as soon as possible [see Warnings and Precautions (5.1)and Use in Specific Populations (8.1)] .

Lactation: Advise nursing women not to breastfeed during treatment with amlodipine besylate and olmesartan medoxomil [see Use in Specific Populations (8.2)] .

Potassium Supplements: Advise patients not to use potassium supplements or salt substitutes containing potassium without consulting their healthcare provider.

Marketed by:

GSMS, Inc.

Camarillo, CA 93012 USA

PRINCIPAL DISPLAY PANEL

NDC 51407-857-30
amlodipine and olmesartan medoxomil
5 mg*/ 20 mg
30 Tablets
Rx only

PACKAGE LABEL

NDC 51407-858-30

amlodipine and olmesartan medoxomil

10 mg*/20 mg

30 Tablets

Rx only

PACKAGE LABEL

NDC 51407-859-30

amlodipine and olmesartan medoxomil

5 mg*/40 mg

30 Tablets

Rx only

PACKAGE LABEL

NDC 51407-860-30

amlodipine and olmesartan medoxomil

10 mg*/40 mg

30 Tablets

Rx only